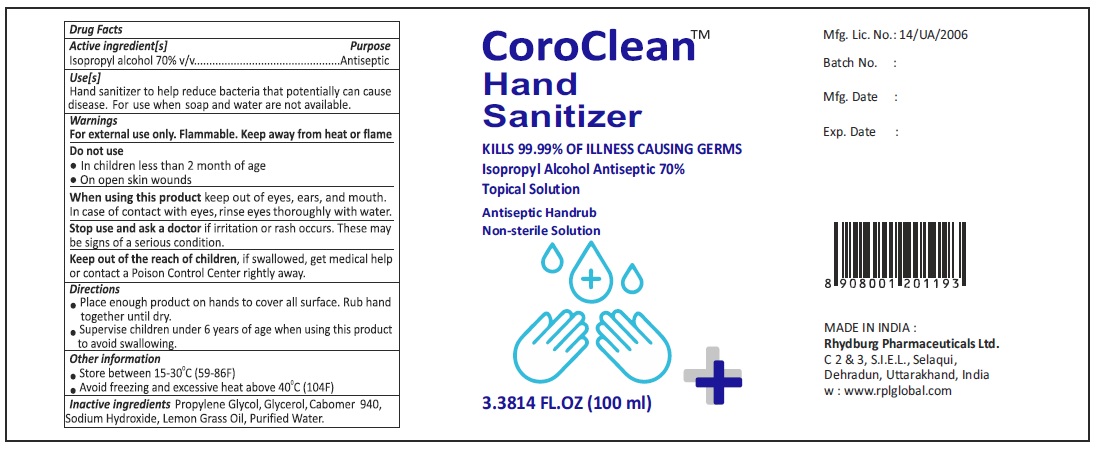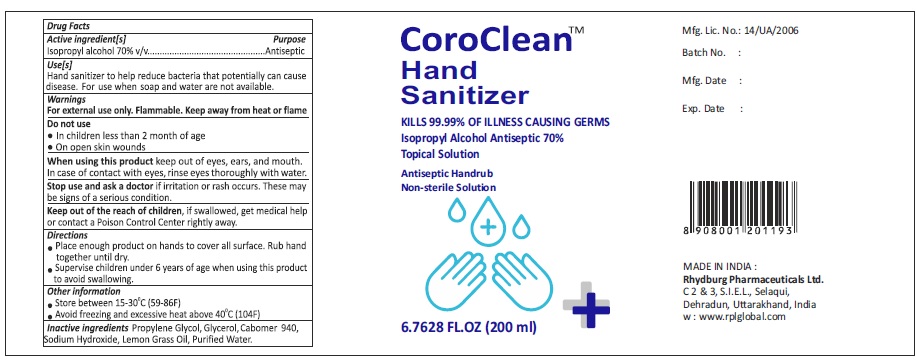 DRUG LABEL: CorocClean Hand Sanitizer
NDC: 78925-001 | Form: LIQUID
Manufacturer: Rhydburg Pharmaceuticals Limited
Category: otc | Type: HUMAN OTC DRUG LABEL
Date: 20210108

ACTIVE INGREDIENTS: ISOPROPYL ALCOHOL 70 mL/100 mL
INACTIVE INGREDIENTS: GLYCERIN 0.5 mL/100 mL; WATER; CARBOMER HOMOPOLYMER TYPE C (ALLYL PENTAERYTHRITOL CROSSLINKED); PROPYLENE GLYCOL 1 mL/100 mL; SODIUM HYDROXIDE; WEST INDIAN LEMONGRASS OIL

The hand sanitizer is manufactured using only the following United States Pharmacopoeia (USP) grade ingredients in the preparation of the product (percentage in final product formulation)

1. Isopropyl Alcohol (70%, v/v)
2. Glycerol (0.5% v/v).
3. Propylene Glycol (1% v/v).
4. Carbomer 940 (0.20% v/v)
5. SodiumHydroxide (0.015% v/v)
6. Lemongrass Oil (INHS) (0.10% v/v)
7. Purified water q. s. to 1 ml

The firm does not add other active or inactive ingredients. Different or additional ingredients may impact the quality and potency of the product.

Active Ingredient(s)

Isopropyl Alcohol 70% v/v. Purpose: Antiseptic

Purpose

Antiseptic, Hand Sanitizer

Use

Hand Sanitizer to help reduce bacteria that potentially can cause disease. For use when soap and water are not available.

Warnings

For external use only. Flammable. Keep away from heat or flame

Do not use

- in children less than 2 months of age
- on open skin wounds

When using this product keep out of eyes, ears, and mouth. In case of contact with eyes, rinse eyes thoroughly with water.
Stop use and ask a doctor if irritation or rash occurs. These may be signs of a serious condition.
Keep out of reach of children. If swallowed, get medical help or contact a Poison Control Center right away.

Stop use and ask a doctor if irritation or rash occurs. These may be signs of a serious condition.

Keep out of reach of children. If swallowed, get medical help or contact a Poison Control Center right away.

Directions

- Place enough product on hands to cover all surfaces. Rub hands together until dry.
- Supervise children under 6 years of age when using this product to avoid swallowing.

Other information

- Store between 15-30C (59-86F)
- Avoid freezing and excessive heat above 40C (104F)

Inactive ingredients

glycerin, Propylene Glycol, Carbomer 940,Sodium Hydroxide,Lemongrass Oil,purified water USP